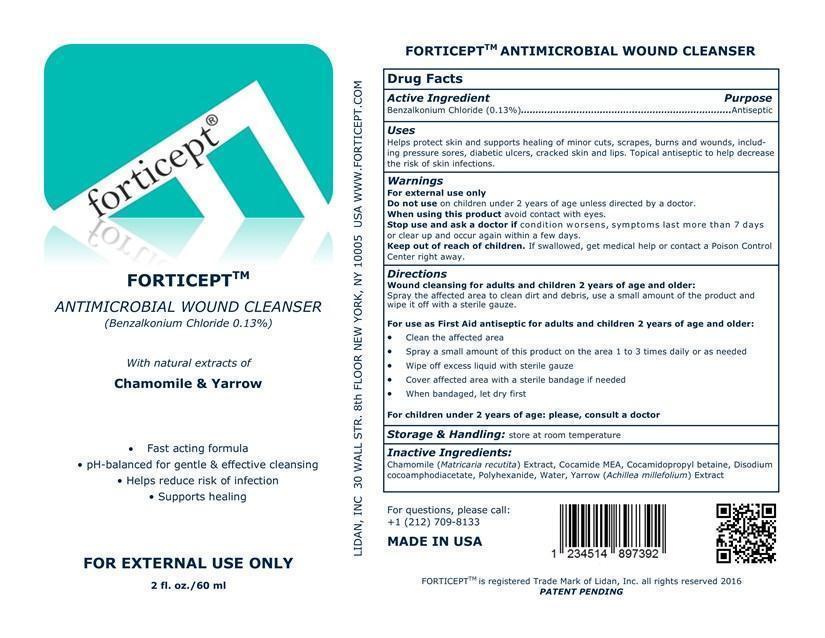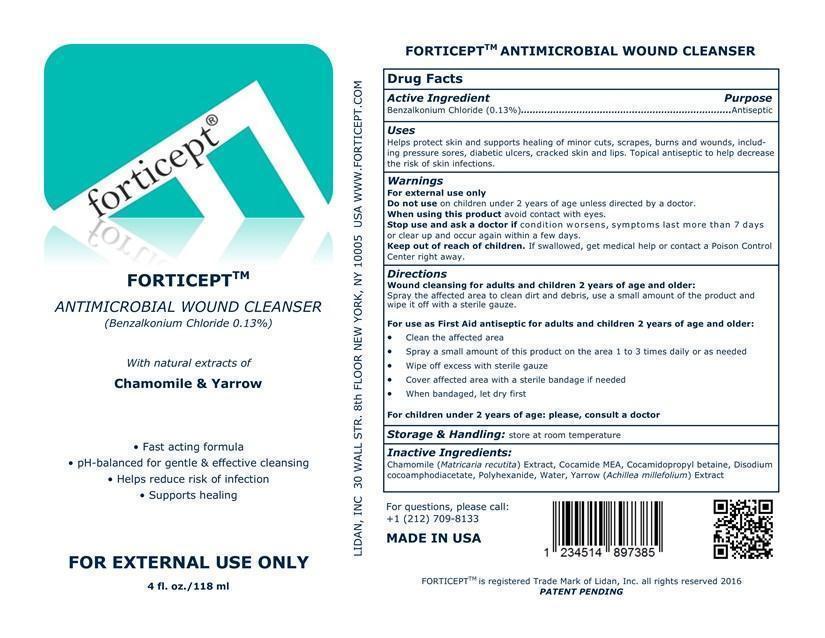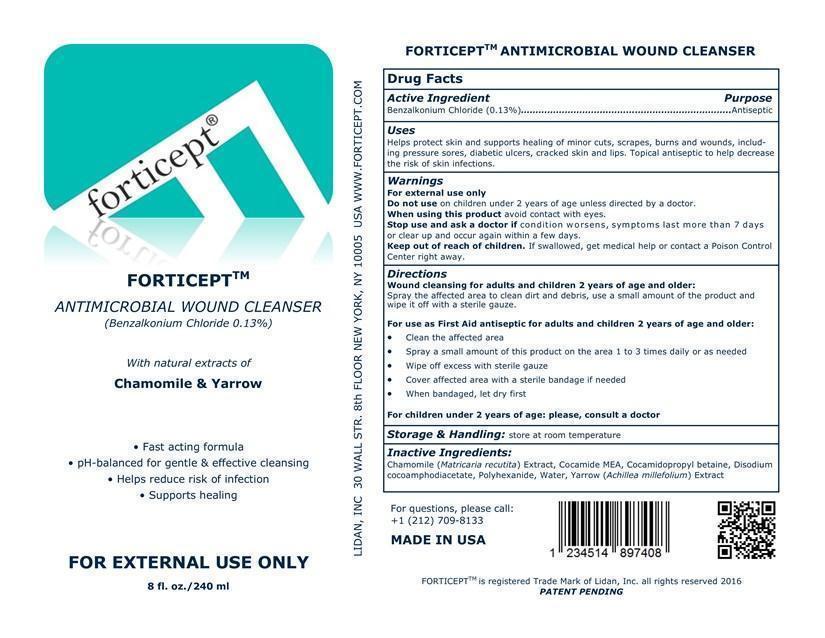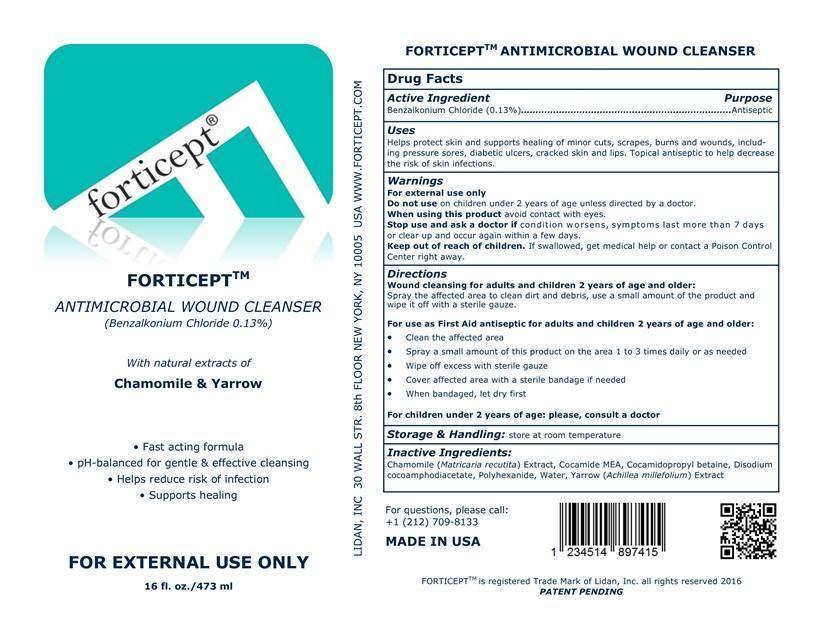 DRUG LABEL: Forticept Antimicrobial Wound Cleanser
NDC: 52261-0700 | Form: LIQUID
Manufacturer: Cosco International, Inc.
Category: otc | Type: HUMAN OTC DRUG LABEL
Date: 20161027

ACTIVE INGREDIENTS: benzalkonium chloride 1.3 g/1000 g
INACTIVE INGREDIENTS: chamomile .1 g/1000 g; COCO MONOETHANOLAMIDE .5 g/1000 g; cocamidopropyl betaine 4 g/1000 g; disodium cocoamphodiacetate 1 g/1000 g; POLIHEXANIDE 4 g/1000 g; water 989.00 g/1000 g; ACHILLEA MILLEFOLIUM .1 g/1000 g

Drug Facts

Active Ingredient/Purpose

Benzakonium Chloride............Antiseptic

Uses

Helps protect skin and supports healing of minor cuts, scrapes, burns and wounds, includ-ing pressure sores, diabetic ulcers, cracked skin and lips. Topical antiseptic to help decrease the risk of skin infections.

Warnings For external use only.

Do not use on children under 2 years of age unless directed by a doctor.

When using this product avoid contact with eyes.

Stop use and ask a doctor if condition worsens, symptoms last more than 7 days or clear up and occur again within a few days.

Keep out of reach of children. If swallowed, get medical help or contact a Poison Control Center right away.

Directions:

Wound cleansing for adults and children 2 years of age and older:

Spray the affected area to clean dirt and debris, use a small amount of the product and wipe it off with a sterile gauze.

For use as First Aid antiseptic for adults and children 2 years of age and older:

- Clean the affected area
- Spray a small amount of this product on the area 1 to 3 times daily or as needed
- Wipe off excess with sterile gauze
- Cover affected area with a sterile bandage if needed
- When bandaged, let dry first

For children under 2 years of age: please, consult a doctor

Storage and handling:

Store at room temperature.

Inactive ingredients:

chamomile, (matricaria recutita) extract, cocamide MEA, cocamidopropyl betaine, disodium cocamphodiacetate, polyhexanide, water, yarrow (achillea millefolium) extract